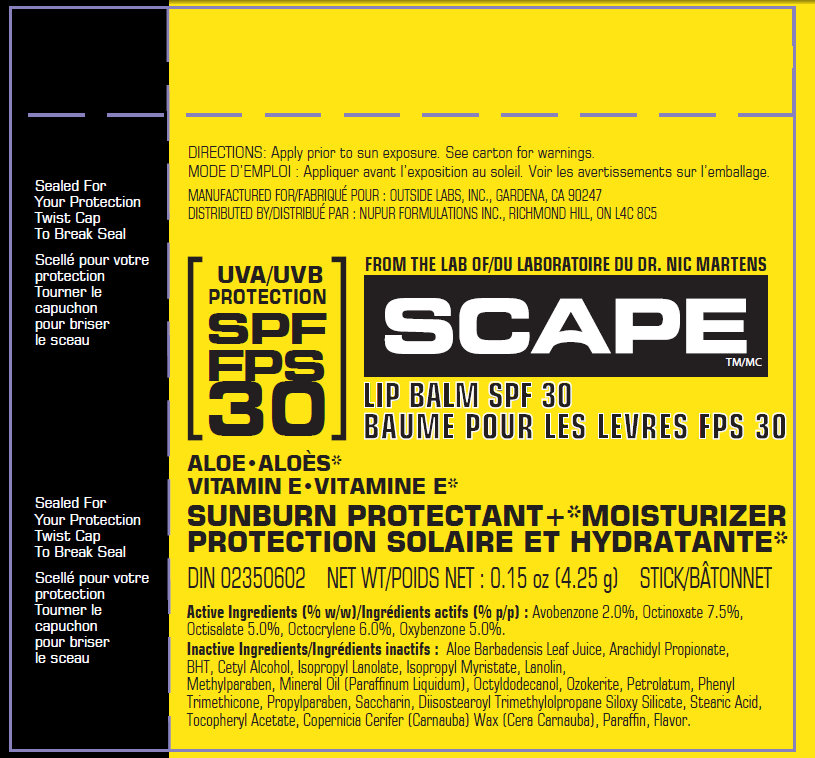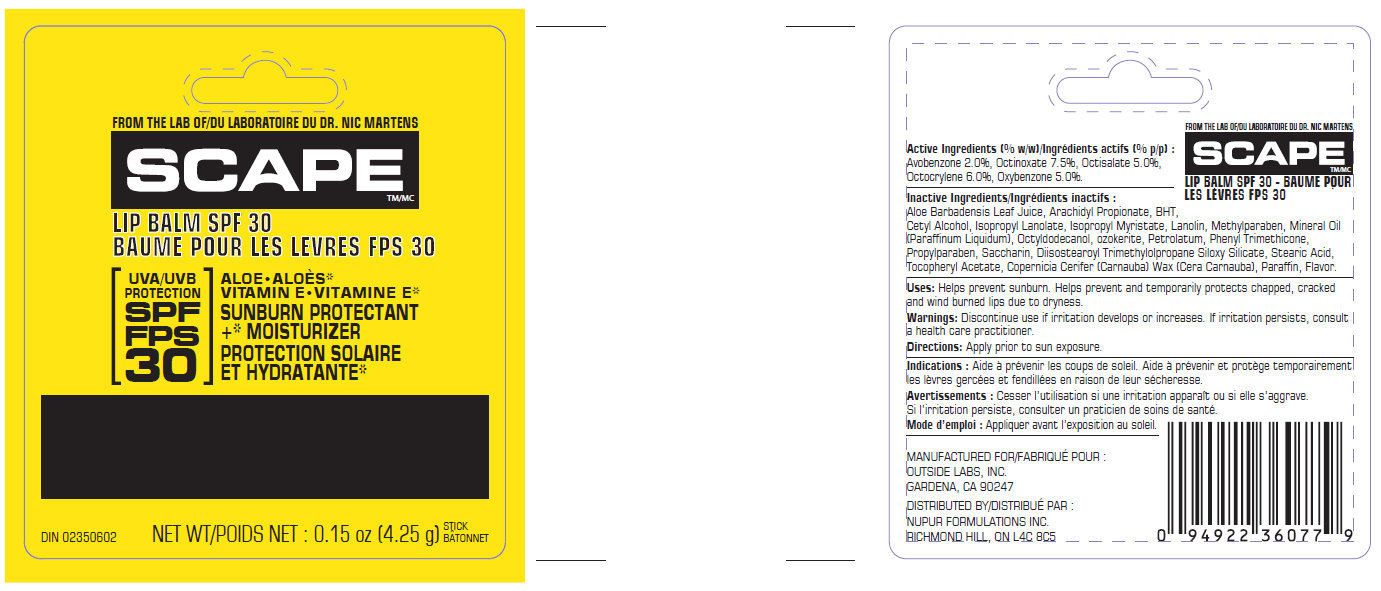 DRUG LABEL: SCAPE SPF 30 LIP BALM
NDC: 76174-140 | Form: STICK
Manufacturer: Nupur Formulations Inc
Category: otc | Type: HUMAN OTC DRUG LABEL
Date: 20110427

ACTIVE INGREDIENTS: AVOBENZONE 2 g/100 g; OCTINOXATE 7.5 g/100 g; OCTISALATE 5 g/100 g; OCTOCRYLENE 6 g/100 g; OXYBENZONE 5 g/100 g
INACTIVE INGREDIENTS: ALOE VERA LEAF; ARACHIDYL PROPIONATE; BUTYLATED HYDROXYTOLUENE; CETYL ALCOHOL; ISOPROPYL MYRISTATE; LANOLIN; METHYLPARABEN; MINERAL OIL; OCTYLDODECANOL; CERESIN; PETROLATUM; PHENYL TRIMETHICONE; PROPYLPARABEN; SACCHARIN; STEARIC ACID; ALPHA-TOCOPHEROL ACETATE; CARNAUBA WAX; PARAFFIN

Scape SPF 30 Lip Balm

FROM THE LAB OF DR. NIC MARTENS

SCAPE

LIP BALM SPF 30

Active Ingredients

Avobenzone 2.0%

Octinoxate 7.5%

Octisalate 5.0%

Octocrylene 6.0%

Oxybenzone 5.0%

Inactive Ingredients:

Aloe Barbadensis Leaf Juice, Arachidyl Propionate, BHT, Cetyl Alcohol, Isopropyl Lanolate, Isopropyl Myristate, Lanolin, Methylparaben, Mineral Oil (Paraffinum Liquidum), Octyldodecanol, Ozokerite, Petrolatum, Phenyl Trimethicone, Propylparaben, Saccharin, Diisostearoyl Trimethylolpropane Siloxy Silicate, Stearic Acid, Tocopheryl Acetate, Copernicia Cenifer (Carnauba) Wax (Cera Carnauba), Paraffin, Flavor.

INDICATIONS AND USAGE

Uses: Helps prevent sunburn. Helps prevent and temporarily protects chapped, cracked and wind burned lips due to dryness.

WARNINGS

Warnings: Discontinue use if irritation develops or increases. If irritation persists, consult a health care practitioner.

DOSAGE AND ADMINISTRATION

Directions: Apply prior to sun exposure.

MANUFACTURED FOR:
OUTSIDE LABS, INC.
GARDENA, CA 90247

PACKAGE LABEL

FROM THE LAB OF DR. NIC MARTENS

SCAPE

LIP BALM SPF 30

UVA/UVB

ALOE

VITAMIN E

SUNBURN PROTECTANT

+ MOISTURIZER

NET WT: 0.15OZ (4.25 g) STICK
Sealed For Your Protection
Twist Cap To Break Seal